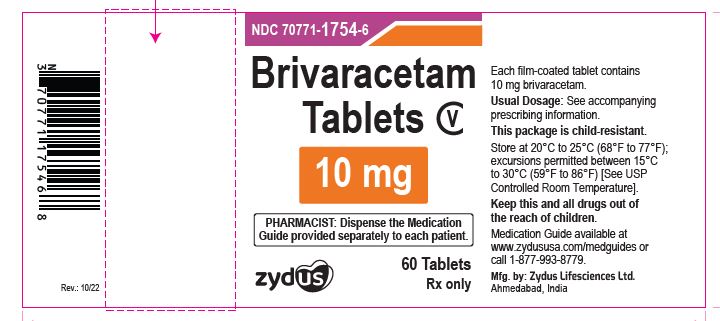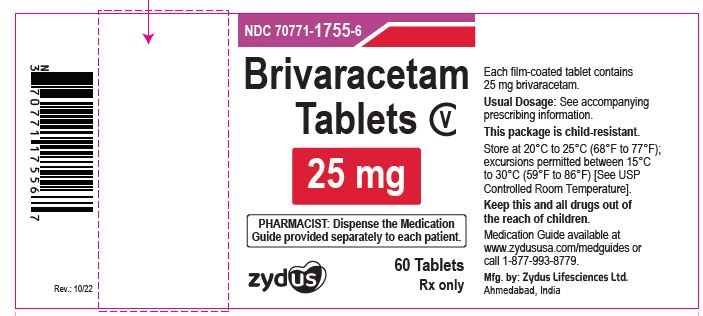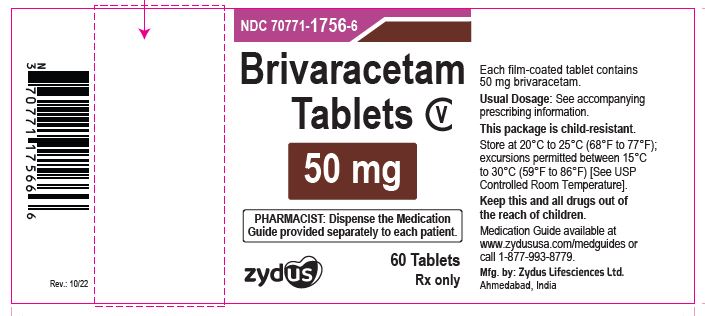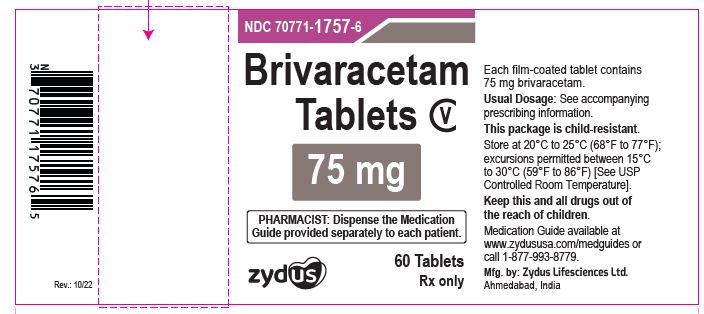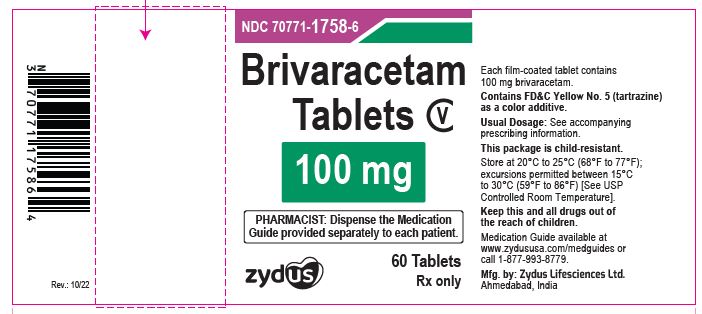 DRUG LABEL: brivaracetam
NDC: 70771-1754 | Form: TABLET, FILM COATED
Manufacturer: Zydus Lifesciences Limited
Category: prescription | Type: HUMAN PRESCRIPTION DRUG LABEL
Date: 20260127
DEA Schedule: CV

ACTIVE INGREDIENTS: BRIVARACETAM 10 mg/1 1
INACTIVE INGREDIENTS: ANHYDROUS LACTOSE; CROSCARMELLOSE SODIUM; GLYCERYL MONO- AND DICAPRYLOCAPRATE; LACTOSE MONOHYDRATE; MAGNESIUM STEARATE; POLYVINYL ALCOHOL, UNSPECIFIED; SODIUM LAURYL SULFATE; TALC; TITANIUM DIOXIDE

BRIVARACETAM tablets, for oral use, CV

PACKAGE LABEL.PRINCIPAL DISPLAY PANEL

NDC 70771-1754-6

Brivaracetam tablets, 10 mg - CV

60 Tablets

Rx only

NDC 70771-1755-6

Brivaracetam tablets, 25 mg - CV

60 Tablets

Rx only

NDC 70771-1756-6

Brivaracetam tablets, 50 mg - CV

60 Tablets

Rx only

NDC 70771-1757-6

Brivaracetam tablets, 75 mg - CV

60 Tablets

Rx only

NDC 70771-1758-6

Brivaracetam tablets, 100 mg - CV

60 Tablets

Rx only